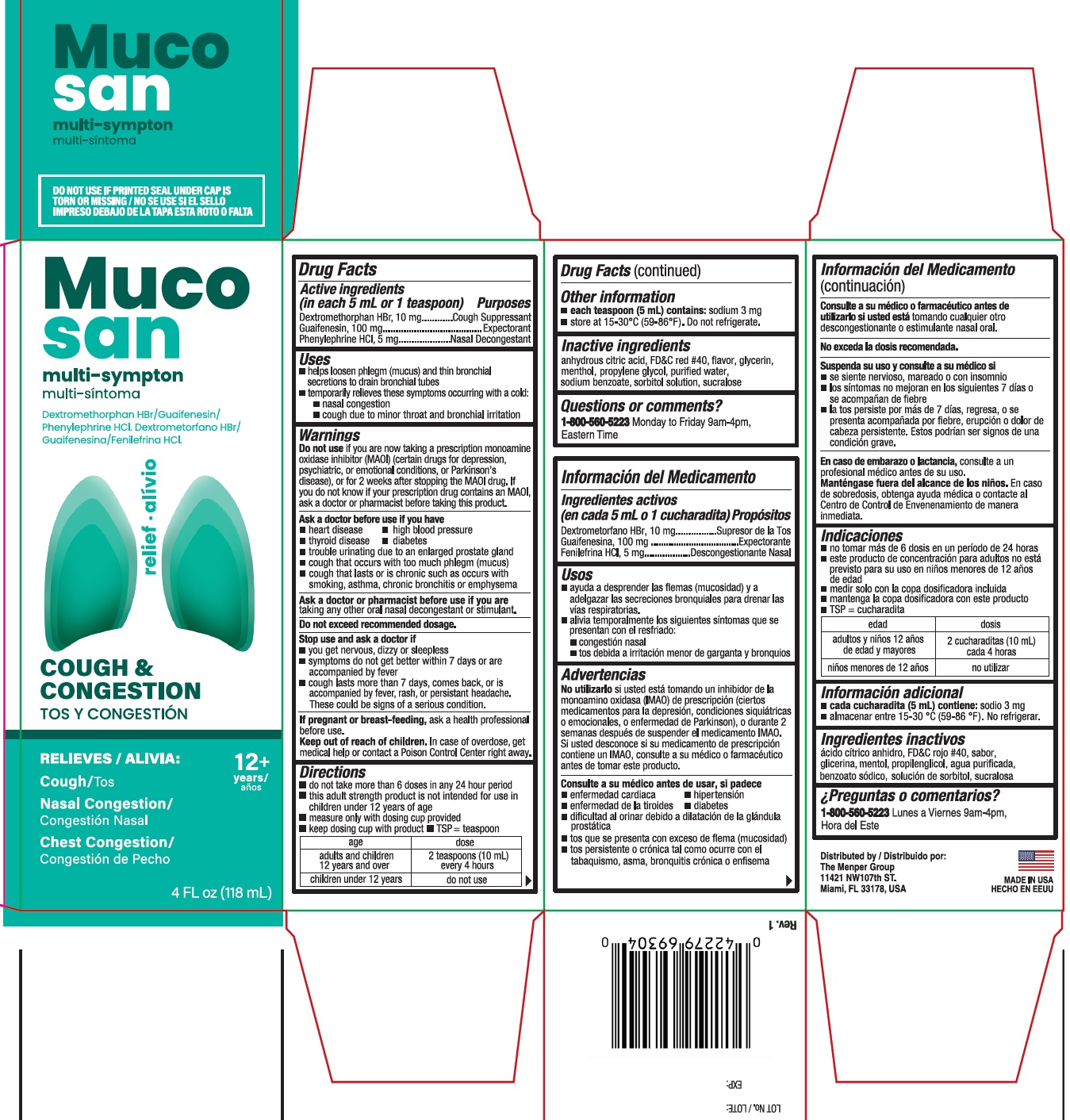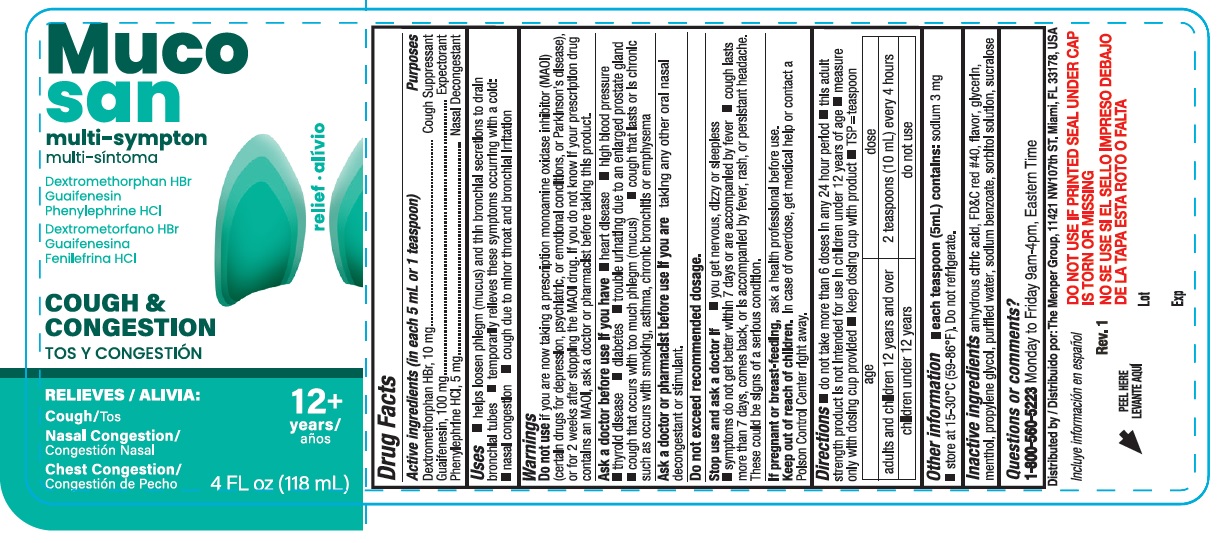 DRUG LABEL: Mucosan Multi-Symptom Cherry
NDC: 53145-693 | Form: LIQUID
Manufacturer: Menper Distributors, Inc.
Category: otc | Type: HUMAN OTC DRUG LABEL
Date: 20260108

ACTIVE INGREDIENTS: DEXTROMETHORPHAN HYDROBROMIDE 10 mg/5 mL; PHENYLEPHRINE HYDROCHLORIDE 5 mg/5 mL; GUAIFENESIN 100 mg/5 mL
INACTIVE INGREDIENTS: SODIUM BENZOATE; WATER; PROPYLENE GLYCOL; ANHYDROUS CITRIC ACID; GLYCERIN; FD&C RED NO. 40; MENTHOL; SORBITOL SOLUTION; SUCRALOSE

Mucosan Multi-Symptom Cherry

INACTIVE INGREDIENT

Active ingredients (in each 5 mL or teaspoon) Purpose

Dextromethorphan HBr, 10 mg..............................Cough suppressant

Guaifenesin, 100 mg..............................................Expectorant

Phenylephrine HCl, 5 mg.......................................Nasal decongestant

Purposes

Cough suppressant

Expectorant

Nasal decongestant

Uses

- helps loosen phlegm (mucus) and thin bronchial secretions to drain bronchial tubes
- temporarily relieves these symptoms occuring with a cold:
- nasal congestion
- cough due to minor throat and bronchial irritation

Warnings

Do not useif you are now taking a prescription monoamine oxidase inhibitor (MAOI) (certain drugs for depression, psychiatric, or emotional conditions, or Parkinson's disease), or for 2 weeks after stopping the MAOI drug. If you do not know if your prescription drug contains an MAOI, ask a doctor or pharmacist before taking this product.

Ask a doctor before use if you have

- heart disease
- high blood pressure
- thyroid disease
- diabetes
- trouble urinating due to an enlarged prostate gland
- cough that occurs with too much phlegm (mucus)
- cough that lasts or is chronic such as occurs with smoking, asthma, chornic bronchitis or emphysema

Ask a doctor or pharmacist before use if you are

taking any other oral nasal decongestant or stimulant.

OVERDOSAGE

Do not exceed recommended dosage.

Stop use and ask a doctor if

- you get nervous, dizzy or sleepless
- symptoms do not get better within 7 days or are accompanied by fever
- cough lasts more than 7 days, comes back, or is accompanied by fever, rash, or persistant headache. These could be signs of a serious condition.

PREGNANCY OR BREAST FEEDING

If pregnant or breast - feeding,ask a helath professional before use.

Keep out of reach of children.In case of overdose, get medical help or contact a Poison Control Center right away.

Directions

- do not take more than 6 doses in any 24 hour period
- this adult stregth product is not intended for use in children under 12 years of age
- measure only with dosing cup provided
- keep dosing cup with product
- TSP=teaspoon

age | dose
adults and children 12 years and over | 2 teaspoons (10mL) every 4 hours
children under 12 years | do not use

Ohter information

- each teaspoon (5mL) contains:sodium 3 mg
- store at 15-30°C (59-86°F). Do not refrigetate.

INACTIVE INGREDIENT

anhydrous citric acid, FD&C red #40, flavor, glycerin, menthol, propylene glycol, purified water, sodium benzoate, sorbitol solution, sucralose

Questions or comments?

1-800-560-5223Monday to Friday 9am-4pm, Eastern Time